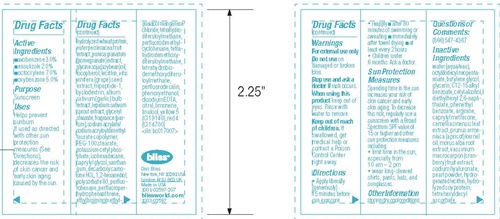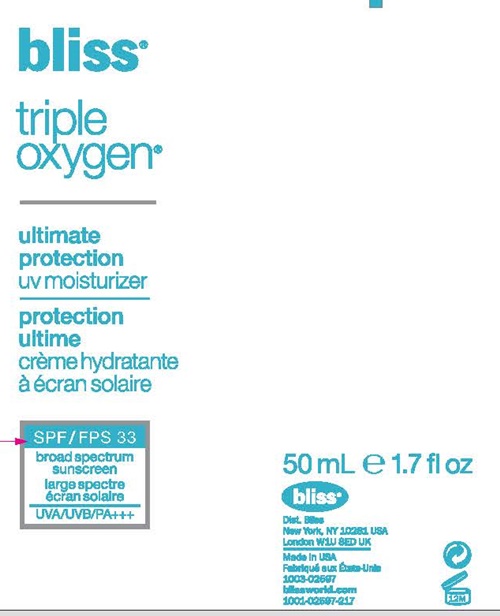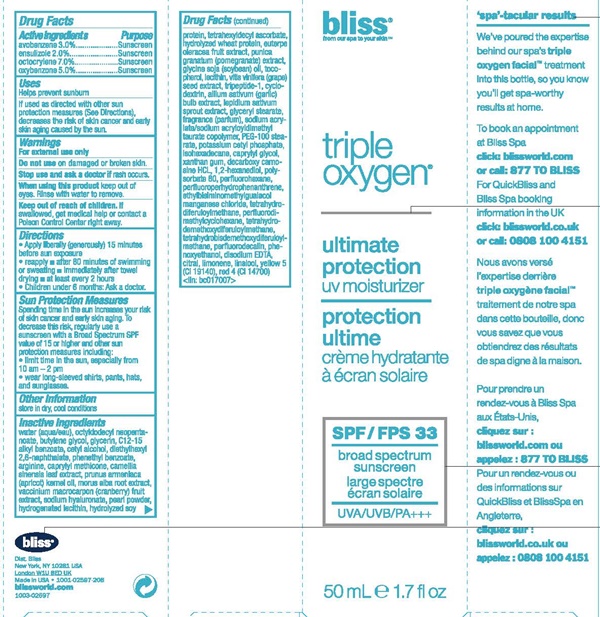 DRUG LABEL: Bliss Triple Oxygen Ultimate Protection UV Moisturizer SPF 33
NDC: 54111-131 | Form: LOTION
Manufacturer: Bentley Laboratories, LLC
Category: otc | Type: HUMAN OTC DRUG LABEL
Date: 20181219

ACTIVE INGREDIENTS: AVOBENZONE 1.5 g/50 mL; ENSULIZOLE 1 g/50 mL; OCTOCRYLENE 3.5 g/50 mL; OXYBENZONE 2.5 g/50 mL
INACTIVE INGREDIENTS: WATER; OCTYLDODECYL NEOPENTANOATE; BUTYLENE GLYCOL; GLYCERIN; ALKYL (C12-15) BENZOATE; CETYL ALCOHOL; DIETHYLHEXYL 2,6-NAPHTHALATE; PHENETHYL BENZOATE; ARGININE; CAPRYLYL TRISILOXANE; GREEN TEA LEAF; APRICOT KERNEL OIL; MORUS ALBA ROOT; CRANBERRY; HYALURONATE SODIUM; PEARL (HYRIOPSIS CUMINGII); HYDROGENATED SOYBEAN LECITHIN; SOY PROTEIN; TETRAHEXYLDECYL ASCORBATE; HYDROLYZED WHEAT PROTEIN (ENZYMATIC, 3000 MW); ACAI; PUNICA GRANATUM ROOT BARK; SOYBEAN OIL; TOCOPHEROL; LECITHIN, SOYBEAN; VITIS VINIFERA SEED; PREZATIDE; BETADEX; GARLIC; GARDEN CRESS SPROUT; GLYCERYL MONOSTEARATE; SODIUM ACRYLATE/SODIUM ACRYLOYLDIMETHYLTAURATE COPOLYMER (4000000 MW); PEG-100 STEARATE; POTASSIUM CETYL PHOSPHATE; ISOHEXADECANE; CAPRYLYL GLYCOL; XANTHAN GUM; DECARBOXY CARNOSINE HYDROCHLORIDE; 1,2-HEXANEDIOL; POLYSORBATE 80; PERFLEXANE; PERFLUOROPERHYDROPHENANTHRENE; ETHYLBISIMINOMETHYLGUAIACOL MANGANESE CHLORIDE; TETRAHYDRODIFERULOYLMETHANE; PERFLUORODIMETHYLCYCLOHEXANE; TETRAHYDRODEMETHOXYDIFERULOYLMETHANE; PERFLUNAFENE; PHENOXYETHANOL; EDETATE SODIUM; CITRAL; LIMONENE, (+)-; LINALOOL, (+)-; BASIC YELLOW 5; SOLVENT RED 4

Bliss Triple Oxygen Ultimate Protection UV Moisturizer SPF 33 - 131

Drug Facts Active ingredients

avobenzene - 3.0%
ensulizole 2.0%
octocrylene 7.0%
oxybenzone 5.0%

Purpose

Sunscreen

Uses

Helps prevent sunburn

If used as directed with other sun protection measures (See Directions), decreases the risk of skin cancer and early skin aging cause by the sun.

Warnings

For external use

Do not use on damaged or broken skin.

Stop use and ask a doctor if rash occurs.

When using this product keep out of eyes. Rinse with water to remove.

Keep out of reach of children.

If swallowed, get medical help or contact a Poison Control Center right away.

Directions

- Apply liberally (generously) 15 minutes before sun exposure
- reapply:
- after 80 minutes of swimming or sweating
- immediately after towel drying
- at least every 2 hours
- Children under 6 months: Ask a doctor

Sun Protection Measures

Spending time in the sun increases your risk of skin cancer and early skin aging. To decrease this risk, regularly use a sunscreen with a Broad Spectrum SPF value of 15 or higher and other sun protection measures including:

- limit time in the sun, especially from 10 am - 2 pm
- wear long sleeved shirts, pants, hats, and sunglasses.

Other information

store in a cool dry place

Inactive Ingredients

water(aqua/eau), octyldodecyl neopentanoate, Butylene glycol, glycerin. C12-15 alkyl benzoate, cetyl alcohol, diethylhexyl 2,6-naphthalate, phenethyl benzoate, arginine, caprylyl methicone, camellia sinensis leaf extract, prunus armeniaca (apricot) kernel oil, morus alba root extract, vaccinium macrocarpon (cranberry) fruit extract, sodium hyaluronate, pearl powder, hydrogenated lecithin, hydrolyzed soy protein, tetrahexyldecyl ascorbate, hydrolyzed wheat protein, euterpe oleracea fruit extract, punica granatum (pomegranate) extract, glycine soja (soybean) oil, tocoherol, lecithin, vitis vinifera (grape) seed extract, tripeptide-1, cyclodextrin, allium sativum (garlic) bulb extract, lepidium sativum sprout extract, glycerly stearate, fragrance (parfum), sodium acrylate/sodium acryloyldimethyl taurate copolymer, PEG-100 stearate, potassium cetyl phosphate, isohexadecane, caprylyl glycol, xanthan gum, decarboxy carnosine HCL, 1,2-hexanediol, polysorbate 80, perfluorohexane, perfluoroperhydrophenanthrene, ethylbisiminomethylguaiacol manganese chloride, tetrahydrodemethoxydiferuloylmethane, tetrahydrobisdemethoxydiferuloylmethane, perfluorodecalin, phenoxyethanol, disodium EDTA, citral, limonene, linallo, yellow 5 (Cl 19140), red 4 (Cl 14700) <iln: bc017007>

Bliss Triple Oxygen Ultimate Protection UV Moisturizer SPF 33 product label

bliss®
from our spa to your skin™
triple oxygen®

ultimate protection
uv moisturizer

SPF 33

broad spectrum sunscreen

UVA/UVB/PA+++

50 mL 1.7 fl oz

"spa"-tacular results

We've poured the expertise behind our spa's triple oxygen facial™ treatment into this bottle, so you know you'll get spa-worthy results at home.

To book an appointment at Bliss Spa click: blissworld.com or call: 877 TO BLISS

For QuickBliss and Bliss Spa booking information in the UK click: bliss world.co.uk or call: 0808 100 4151

bliss®

Dist. Bliss
New York, NY 10281 USA
London W1U 8ED UK
Made in the USA • 1001-02597-208
blissworld.com
1003-02597